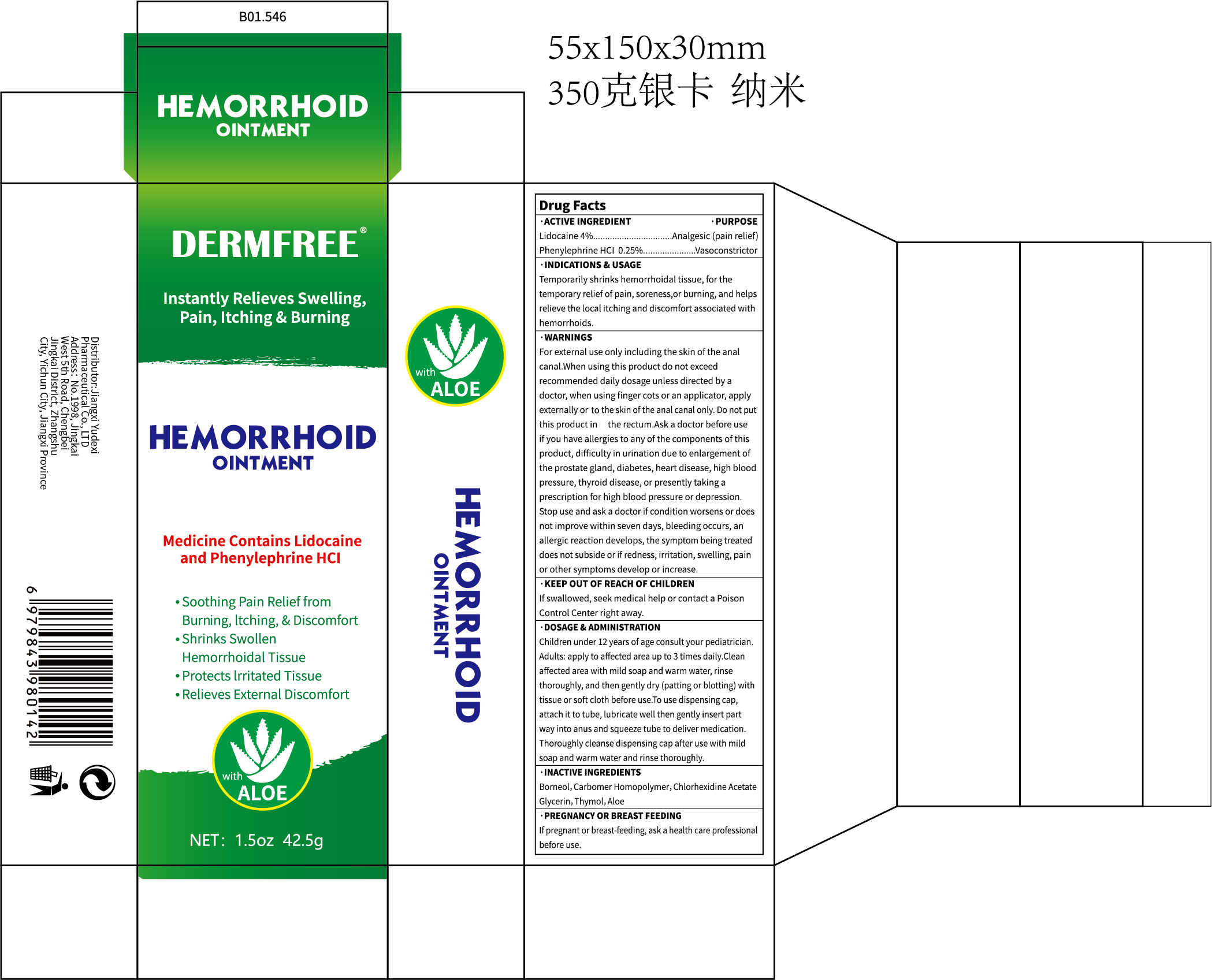 DRUG LABEL: DERMFREE HEMORRHOID
NDC: 85248-127 | Form: CREAM
Manufacturer: Jiangxi Yudexi Pharmaceutical Co., LTD
Category: otc | Type: HUMAN OTC DRUG LABEL
Date: 20260208

ACTIVE INGREDIENTS: LIDOCAINE 4 g/100 g; PHENYLEPHRINE HYDROCHLORIDE 0.25 g/100 g
INACTIVE INGREDIENTS: CARBOMER HOMOPOLYMER, UNSPECIFIED TYPE; CHLORHEXIDINE ACETATE; GLYCERIN; BORNEOL; THYMOL; ALOE

85248-127

Active Ingredient

Lidocaine 4% Phenylephrine HCl 0.25%

Purpose

Analgesic (pain relief) Vasoconstrictor

Use

For external use only including the skin of the anal canal

Warnings

When using this product do not exceed recommended daily dosage unless directed by a doctor, when using finger cots or an applicator, apply externally or to the skin of the anal canal only. Do not put this product into the rectum.

Do not use

Children under 12 years of age consult your pediatrician.

When Using

When using this product do not exceed recommended daily dosage unless directed by a doctor, when using finger cots or an applicator, apply externally or to the skin of the anal canal only. Do not put this product into the rectum.

Stop Use

Ask a doctor before use if you have allergies to any of the components of this product, difficulty in urination due to enlargement of the prostate gland, diabetes, heart disease, high blood pressure, thyroid disease, or presently taking a prescription for high blood pressure or depression.

Ask Doctor

Stop use and ask a doctor if condition worsens or does not improve
within seven days, bleeding occurs, an allergic reaction develops, the
symptom being treated does not subside or if redness, irritation, swelling, pain or other symptoms develop or increase.

Keep Oot Of Reach Of Children

If swallowed, seek medical help or contact a Poison Control Center right away.

Directions

Adults: apply to affected area up to 3 times daily.Clean affected area with mild soap and warm water, rinse thoroughly, and then gently dry (patting or blotting) with tissue or soft cloth before use.
To use dispensing cap, attach it to tube, lubricate well then gently insert part way into anus and squeeze tube to deliver medication. Thoroughly cleanse dispensing cap after use with mild soap and warm water and rinse thoroughly.

Other information

If pregnant or breast-feeding, ask a health care professional before use.

Inactive ingredients

Borneol,Carbomer Homopolymer,Chlorhexidine Acetate ，Glycerin, Thymol, Aloe